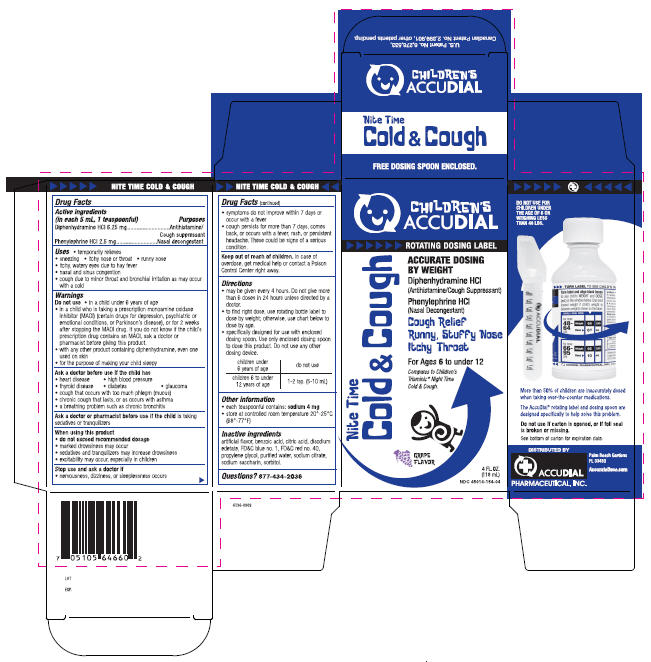 DRUG LABEL: Nite Time Cold and Cough
NDC: 45014-154 | Form: LIQUID
Manufacturer: Accudial Pharmaceutical, Inc.
Category: otc | Type: HUMAN OTC DRUG LABEL
Date: 20091111

ACTIVE INGREDIENTS: Diphenhydramine Hydrochloride 6.25 mg/5 mL; Phenylephrine Hydrochloride 2.5 mg/5 mL
INACTIVE INGREDIENTS: Grape; Benzoic Acid; Citric Acid Monohydrate; Edetate Disodium; FD&C BLUE NO. 1; FD&C RED NO. 40; Propylene Glycol; Water; Sodium Citrate; Saccharin Sodium; Sorbitol

Children's
ACCUDIAL

NITE TIME COLD & COUGH

Drug Facts

ACTIVE INGREDIENT

PURPOSE

Active ingredients (in each 5 mL, 1 teaspoonful) | Purposes
Diphenhydramine HCl 6.25 mg | Antihistamine/Cough suppressant
Phenylephrine HCl 2.5 mg | Nasal decongestant

Uses

- temporarily relieves
- sneezing
- itchy nose or throat
- runny nose
- itchy, watery eyes due to hay fever
- nasal and sinus congestion
- cough due to minor throat and bronchial irritation as may occur with a cold

Warnings

Do not use

- in a child under 6 years of age
- in a child who is taking a prescription monoamine oxidase inhibitor (MAOI) (certain drugs for depression, psychiatric or emotional conditions, or Parkinson's disease), or for 2 weeks after stopping the MAOI drug. If you do not know if the child's prescription drug contains an MAOI, ask a doctor or pharmacist before giving this product.
- with any other product containing diphenhydramine, even one used on skin
- for the purpose of making your child sleepy

Ask a doctor before use if the child has

- heart disease
- high blood pressure
- thyroid disease
- diabetes
- glaucoma
- cough that occurs with too much phlegm (mucus)
- chronic cough that lasts, or as occurs with asthma
- a breathing problem such as chronic bronchitis

Ask a doctor or pharmacist before use if the child is taking sedatives or tranquilizers

When using this product

- do not exceed recommended dosage
- marked drowsiness may occur
- sedatives and tranquilizers may increase drowsiness
- excitability may occur, especially in children

Stop use and ask a doctor if

- nervousness, dizziness, or sleeplessness occurs
- symptoms do not improve within 7 days or occur with a fever
- cough persists for more than 7 days, comes back, or occurs with a fever, rash, or persistent headache. These could be signs of a serious condition.

Keep out of reach of children. In case of overdose, get medical help or contact a Poison Control Center right away.

Directions

- may be given every 4 hours. Do not give more than 6 doses in 24 hours unless directed by a doctor.
- to find right dose, use rotating bottle label to dose by weight; otherwise, use chart below to dose by age.
- specifically designed for use with enclosed dosing spoon. Use only enclosed dosing spoon to dose this product. Do not use any other dosing device.

children under 6 years of age | do not use
children 6 to under 12 years of age | 1-2 tsp. (5-10 mL)

Other information

- each teaspoonful contains: sodium 4 mg
- store at controlled room temperature 20°-25°C (68°-77°F)

Inactive ingredients

artificial flavor, benzoic acid, citric acid, disodium edetate, FD&C blue no. 1, FD&C red no. 40, propylene glycol, purified water, sodium citrate, sodium saccharin, sorbitol.

Questions?

877-434-2036

PRINCIPAL DISPLAY PANEL - 118 mL Carton

CHILDREN'S
ACCUDIAL

ROTATING DOSING LABEL

Nite Time
Cold & Cough

ACCURATE DOSING
BY WEIGHT

Diphenhydramine HCl
(Antihistamine/Cough Suppressant

Phenylephrine HCl
(Nasal Decongestant)

Cough Relief
Runny, Stuffy Nose
Itchy Throat

For Ages 6 to under 12

Compares to Children's
Triaminic® Night Time
Cold & Cough.

GRAPE
FLAVOR

4 FL. OZ.
(118 mL)
NDC 45014-154-04